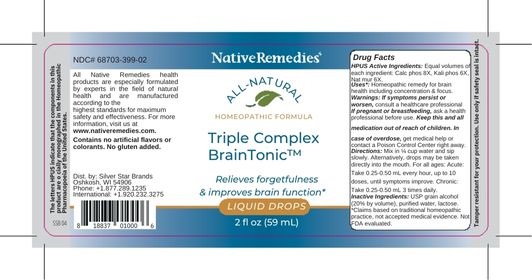 DRUG LABEL: NativeRemedies Triple Complex Brain Tonic
NDC: 68703-399 | Form: LIQUID
Manufacturer: Silver Star Brands
Category: homeopathic | Type: HUMAN OTC DRUG LABEL
Date: 20250101

ACTIVE INGREDIENTS: POTASSIUM PHOSPHATE, DIBASIC 6 [hp_X]/59 mL; CALCIUM PHOSPHATE 8 [hp_X]/59 mL; SODIUM CHLORIDE 6 [hp_X]/59 mL
INACTIVE INGREDIENTS: ALCOHOL; SUCROSE; WATER

NativeRemedies® Triple Complex Brain Tonic™

HPUS Active Ingredients: Equal volumes of each ingredinet: Calc phos 8X, Kali phos 6X, Nat mur 6X.

The letters HPUS indicate that the components in this product are officially monographed in the Homeopathic Pharmacopoeia of the United States.

Uses*

Uses*: Homeopathic remedy for brain health including concentration & focus.

*Claims based on traditional homeopathic practice, not accepted medical evidence. Not FDA evaluated.

Warnings

Warnings: If symptoms persist or worsen, consult a health professional. If pregnant or breastfeeding, ask a health professional before use. Keep this and all medication out of reach of children. In case of overdose, get medical help or contact a Poison Control Center right away.

Directions

Directions: Mix in 1/4 cup water and sip slowly. Alternatively, drops may be taken directly into the mouth. For all ages: Acute: Take 0.25-0.50 mL every hour, up to 10 doses, until symptoms imporve. Chronic: Take 0.25-0.50 mL 3 times daily.

OTHER SAFETY INFORMATION

Contains no artificial flavors or colorants. No gluten added.

Tamper resistant for your protection. Use only if safety seal is intact.

Inactive Ingredients

Inactive Ingredients: USP grain alcohol (20% by volume), purified water, sucrose.

KEEP OUT OF REACH OF CHILDREN

Keep this and all medications out of reach of children.

PREGNANCY OR BREAST FEEDING

If pregnant or breastfeeding, ask a health professional before use.

PURPOSE

Relieves forgetfulness & improves brain function.